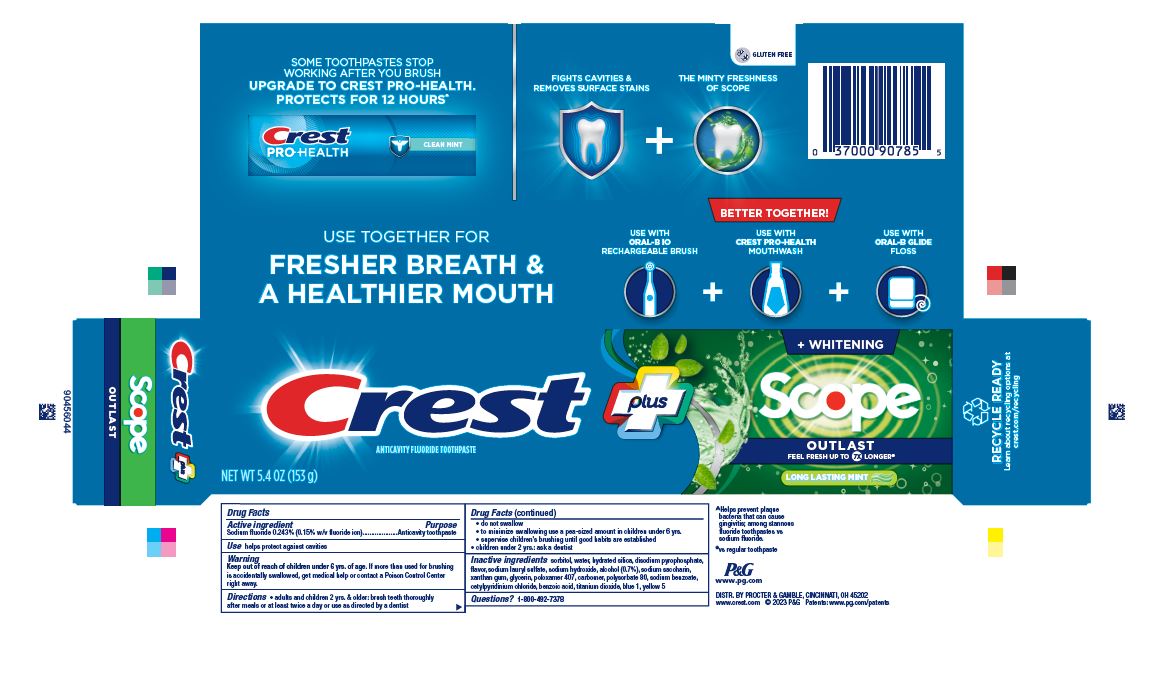 DRUG LABEL: Crest Complete plus
NDC: 37000-445 | Form: PASTE, DENTIFRICE
Manufacturer: The Procter & Gamble Manufacturing Company
Category: otc | Type: HUMAN OTC DRUG LABEL
Date: 20260212

ACTIVE INGREDIENTS: SODIUM FLUORIDE 1.5 mg/1 g
INACTIVE INGREDIENTS: SODIUM HYDROXIDE; SACCHARIN SODIUM; GLYCERIN; POLOXAMER 407; SODIUM ACID PYROPHOSPHATE; SODIUM LAURYL SULFATE; ALCOHOL; XANTHAN GUM; CARBOXYPOLYMETHYLENE; POLYSORBATE 80; SODIUM BENZOATE; CETYLPYRIDINIUM CHLORIDE; SORBITOL; BENZOIC ACID; FD&C BLUE NO. 1; WATER; HYDRATED SILICA; TITANIUM DIOXIDE; FD&C YELLOW NO. 5

Crest®
plus™
Whitening
Scope Outlast®

Drug Facts

Active ingredient

Sodium fluoride 0.243%

(0.15% w/v fluoride ion)

Purpose

Anticavity toothpaste

Use

helps protect against cavities

Warnings

Keep out of reach of children under 6 yrs. of age. If more than used for brushing is accidentally swallowed, get medical help or contact a Poison Control Center right away.

Directions

- adults and children 2 yrs. & older: brush teeth thoroughly after meals or at least twice a day or use as directed by a dentist
  - do not swallow
  - to minimize swallowing use a pea-sized amount in children under 6
  - supervise children's brushing until good habits are established
- children under 2 yrs.: ask a dentist

Inactive ingredients

sorbitol, water, hydrated silica, disodium pyrophosphate, flavor, sodium lauryl sulfate, sodium hydroxide, alcohol (0.7%), xanthan gum, sodium saccharin, glycerin, carbomer, poloxamer 407, polysorbate 80, sodium benzoate, cetylpyridinium chloride, benzoic acid, titanium dioxide, blue 1, yellow 5

Questions?

1-800-492-7378

DISTR. BY PROCTER & GAMBLE,
CINCINNATI, OH 45202

PRINCIPAL DISPLAY PANEL - 153 g Carton

Crest ®

plus™

NET WT 5.4 OZ (153 g)

FLUORIDE TOOTHPASTE
+ WHITENING
scope
OUTLAST ®

FEEL FRESH UP TO 7X LONGER

long lasting mint